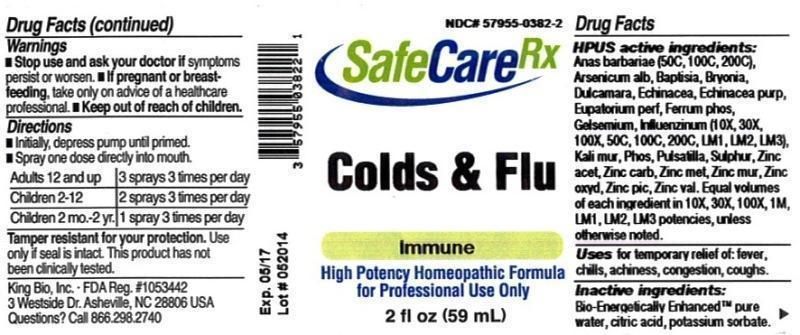 DRUG LABEL: Colds and Flu
NDC: 57955-0382 | Form: LIQUID
Manufacturer: King Bio Inc.
Category: homeopathic | Type: HUMAN OTC DRUG LABEL
Date: 20150305

ACTIVE INGREDIENTS: CAIRINA MOSCHATA HEART/LIVER AUTOLYSATE 50 [hp_C]/59 mL; ARSENIC TRIOXIDE 10 [hp_X]/59 mL; BAPTISIA TINCTORIA ROOT 10 [hp_X]/59 mL; BRYONIA ALBA ROOT 10 [hp_X]/59 mL; SOLANUM DULCAMARA TOP 10 [hp_X]/59 mL; ECHINACEA, UNSPECIFIED 10 [hp_X]/59 mL; ECHINACEA PURPUREA 10 [hp_X]/59 mL; EUPATORIUM PERFOLIATUM FLOWERING TOP 10 [hp_X]/59 mL; FERROSOFERRIC PHOSPHATE 10 [hp_X]/59 mL; GELSEMIUM SEMPERVIRENS ROOT 10 [hp_X]/59 mL; INFLUENZA A VIRUS 50 [hp_C]/59 mL; INFLUENZA B VIRUS 50 [hp_C]/59 mL; POTASSIUM CHLORIDE 10 [hp_X]/59 mL; PHOSPHORUS 10 [hp_X]/59 mL; PULSATILLA VULGARIS 10 [hp_X]/59 mL; SULFUR 10 [hp_X]/59 mL; ZINC ACETATE ANHYDROUS 10 [hp_X]/59 mL; ZINC CARBONATE 10 [hp_X]/59 mL; ZINC 10 [hp_X]/59 mL; ZINC CHLORIDE 10 [hp_X]/59 mL; ZINC OXIDE 10 [hp_X]/59 mL; ZINC PICRATE NONAHYDRATE 10 [hp_X]/59 mL; ZINC VALERATE DIHYDRATE 10 [hp_X]/59 mL
INACTIVE INGREDIENTS: WATER; POTASSIUM SORBATE; ANHYDROUS CITRIC ACID

Colds and Flu

ACTIVE INGREDIENT

Drug Facts__________________________________________________________________________________________________________

HPUS active ingredients: Anas barbariae (50C, 100C, 200C), Arsenicum album, Baptisia tinctoria, Bryonia, Dulcamara, Echinacea, Echinacea purpurea, Eupatorium perfoliatum, Ferrum phosphoricum, Gelsemium sempervirens, Influenzinum (10X, 30X, 100X, 50C, 100C, 200C, LM1, LM2, LM3), Kali muriaticum, Phosphorus, Pulsatilla, Sulphur, Zincum aceticum, Zincum carbonicum, Zincum metallicum, Zincum muriaticum, Zincum oxydatum, Zincum picricum, Zincum valerianicum. Equal volumes of each ingredient in 10X, 30X, 100X, 1M, LM1, LM2, LM3 potencies, unless otherwise noted.

INDICATIONS AND USAGE

Uses for temporary relief of: fever, chills, achiness, congestion, coughs.

Inactive Ingredients:

Bio-Energetically Enhanced™ pure water, citric acid and potassium sorbate.

Warnings

- Stop use and ask your doctor if symptoms persist or worsen.
- If pregnant or breast-feeding, take only on advice of a healthcare professional.

- Keep out of reach of children.

Directions

- Initially, depress pump until primed.
- Spray one dose directly into mouth.
- Adults 12 and up: 3 sprays 3 times per day
- Children 2-12: 2 sprays 3 times per day
- Children 2 mo.-2 yr: 1 spray 3 times per day

OTHER SAFETY INFORMATION

Tamper resistant for your protection. Use only if safety seal is intact. This product has not been clinically tested.

Uses:

- fever
- chills
- achiness
- congestion
- coughs